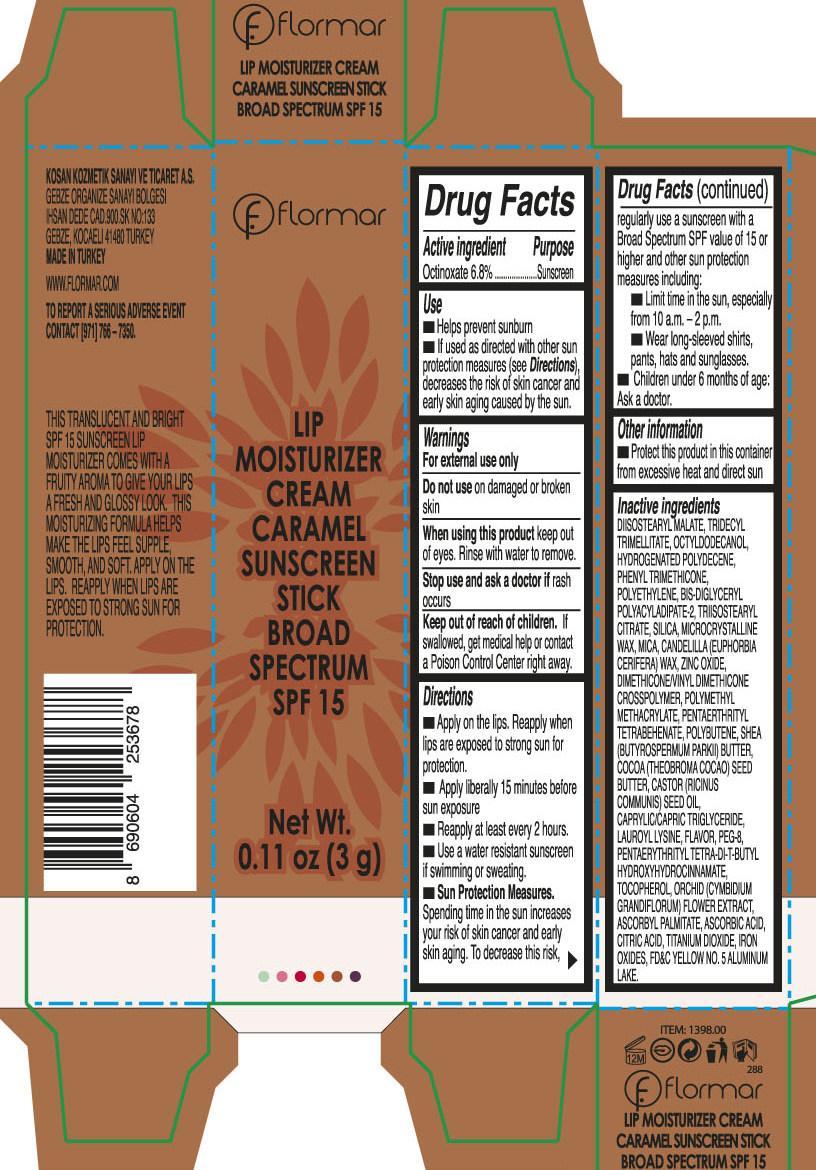 DRUG LABEL: Flormar Lip Moisturizer Cream Carmel Sunscreen Broad Spectrum SPF 15
NDC: 61722-253 | Form: STICK
Manufacturer: Kosan Kozmetik Sanayi ve Ticaret A.S.
Category: otc | Type: HUMAN OTC DRUG LABEL
Date: 20191018

ACTIVE INGREDIENTS: OCTINOXATE 68 mg/1 g
INACTIVE INGREDIENTS: DIISOSTEARYL MALATE; TRIDECYL TRIMELLITATE; OCTYLDECANOL; PHENYL TRIMETHICONE; HIGH DENSITY POLYETHYLENE; TRIISOSTEARYL CITRATE; SILICON DIOXIDE; MICROCRYSTALLINE WAX; MICA; ZINC OXIDE; MEDIUM-CHAIN TRIGLYCERIDES; LAUROYL LYSINE; POLYETHYLENE GLYCOL 400; PENTAERYTHRITOL TETRAKIS(3-(3,5-DI-TERT-BUTYL-4-HYDROXYPHENYL)PROPIONATE); TOCOPHEROL; ASCORBYL PALMITATE; ASCORBIC ACID; CITRIC ACID MONOHYDRATE; TITANIUM DIOXIDE; FERRIC OXIDE RED; D&C RED NO. 6

Flormar Lip Moisturizer Cream Carmel Sunscreen Stick Broad Spectrum SPF 15

Active ingredient

Octinoxate 6.8%

Purpose

Sunscreen

Use

- Helps prevent sunburn
- If used as directed with other sun protection measures (see Directions), decreases the risk of skin cancer and early skin aging caused by the sun.

Warnings

For external use only

Do not use

on damaged or broken skin

When using this product

keep out of eyes. Rinse with water to remove.

Stop use and ask a doctor if

rash occurs

Keep out of reach of children

If swallowed, get medical help or contact a Poison Control Center right away.

Directions

- Apply on the lips. Reapply when lips are exposed to strong sun for protection.
- Apply liberally 15 minutes before sun exposure
- Reapply at least every 2 hours.
- Use a water resistant sunscreen if swimming or sweating.
- Sun Protection Measures. Spending time in the sun increases your risk of skin cancer and early skin aging. To decrease this risk, regularly use a sunscreen with a Broad Spectrum SPF value of 15 or higher and other sun protection measures including:

• Limit time in the sun, especially from 10 a.m. - 2 p.m.

• Wear long-sleeved shirts, pants, hats and sunglasses.

• Children under 6 months of age: Ask a doctor.

Other information

Protect this product in this container from excessive heat and direct sun

Inactive ingredients

DIISOSTEARYL MALATE, TRIDECYL TRIMELLITATE, OCTYLDODECANOL, HYDROGENATED POLYDECENE, PHENYL TRIMETHICONE, POLYETHYLENE, BIS-DIGLYCERYL POLYACYLADIPATE-2, TRIISOSTEARYL CITRATE, SILICA, MICROCRYSTALLINE WAX, MICA, CANDELILLA (EUPHORBIA CERIFERA) WAX, ZINC OXIDE, DIMETHICONE/VINYL DIMETHICONE CROSSPOLYMER, POLYMETHYL METHACRYLATE, PENTAERTHRITYL TETRABEHENATE, POLYBUTENE, SHEA (BUTYROSPERMUM PARKII) BUTTER, COCOA (THEOBROMA COCAO) SEED BUTTER, CASTOR (RICINUS COMMUNIS) SEED OIL, CAPRYLIC/CAPRIC TRIGLYCERIDE, LAUROYL LYSINE, FLAVOR, PEG-8, PENTAERYTHRITYL TETRA-DI-T-BUTYL HYDROXYHYDROCINNAMATE, TOCOPHEROL, ORCHID (CYMBIDIUM GRANDIFLORUM) FLOWER EXTRACT, ASCORBYL PALMITATE, ASCORBIC ACID, CITRIC ACID, TITANIUM DIOXIDE, IRON OXIDES, D&C RED NO. 6., FD&C YELLOW NO.5 ALUMINUM LAKE.